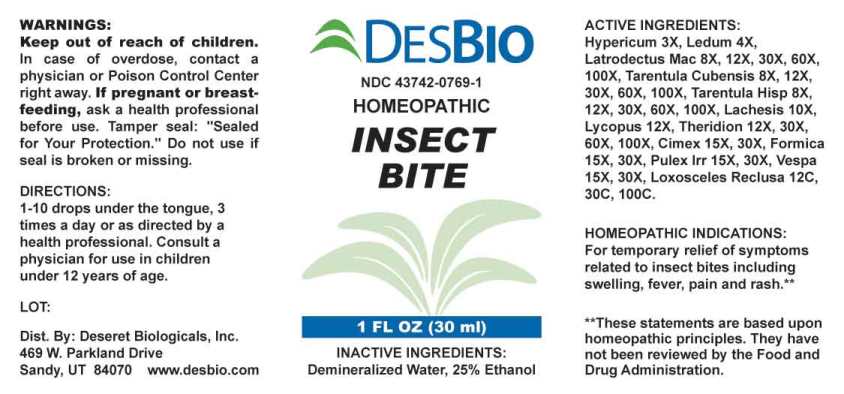 DRUG LABEL: Insect Bite
NDC: 43742-0769 | Form: LIQUID
Manufacturer: Deseret Biologicals, Inc.
Category: homeopathic | Type: HUMAN OTC DRUG LABEL
Date: 20240911

ACTIVE INGREDIENTS: HYPERICUM PERFORATUM WHOLE 3 [hp_X]/1 mL; LEDUM PALUSTRE TWIG 4 [hp_X]/1 mL; LATRODECTUS MACTANS 8 [hp_X]/1 mL; CITHARACANTHUS SPINICRUS 8 [hp_X]/1 mL; LYCOSA TARANTULA 8 [hp_X]/1 mL; LACHESIS MUTA VENOM 10 [hp_X]/1 mL; LYCOPUS VIRGINICUS 12 [hp_X]/1 mL; THERIDION CURASSAVICUM 12 [hp_X]/1 mL; CIMEX LECTULARIUS 15 [hp_X]/1 mL; FORMICA RUFA 15 [hp_X]/1 mL; PULEX IRRITANS 15 [hp_X]/1 mL; VESPA CRABRO 15 [hp_X]/1 mL; LOXOSCELES RECLUSA 12 [hp_C]/1 mL
INACTIVE INGREDIENTS: WATER; ALCOHOL

Drug Facts:

ACTIVE INGREDIENTS:

Hypericum Perforatum 3X, Ledum Palustre 4X, Latrodectus Mactans 8X, 12X, 30X, 60X, 100X, Tarentula Cubensis 8X, 12X, 30X, 60X, 100X, Tarentula Hispana 8X, 12X, 30X, 60X, 100X, Lachesis Mutus 10X, Lycopus Virginicus 12X, Theridion 12X, 30X, 60X, 100X, Cimex Lectularius 15X, 30, Formica Rufa 15X, 30, Pulex Irritans 15X, 30, Vespa Crabro 15X, 30, Loxosceles Reclusa 12C, 30C, 100C.

HOMEOPATHIC INDICATIONS:

For temporary relief of symptoms related to insect bites including swelling, fever, pain and rash.**

**These statements are based upon traditional homeopathic principles. They have not been reviewed by the Food and Drug Administration.

WARNINGS:

Keep out of reach of children. In case of overdose, contact a physician or Poison Control Center right away.

If pregnant or breast-feeding, ask a health professional before use.

Tamper seal: "Sealed for Your Protection." Do not use if seal is broken or missing.

Keep out of reach of children. In case of overdose, contact a physician or Poison Control Center right away.

DIRECTIONS:

1-10 drops under the tongue, 3 times a day or as directed by a health professional. Consult a physician for use in children under 12 years of age.

HOMEOPATHIC INDICAITONS:

For temporary relief of symptoms related to insect bites including swelling, fever, pain and rash.**

**These statements are based upon traditional homeopathic principles. They have not been reviewed by the Food and Drug Administration.

INACTIVE INGREDIENTS:

Demineralized Water, 25% Ethanol

QUESTIONS:

Dist. By: Deseret Biologicals, Inc.
469 W. Parkland Drive
Sandy, UT 84070 www.desbio.com

PACKAGE LABEL DISPLAY:

DESBIO

NDC 43742-0769-1

HOMEOPATHIC

INSECT BITE

1 FL OZ (30 ml)